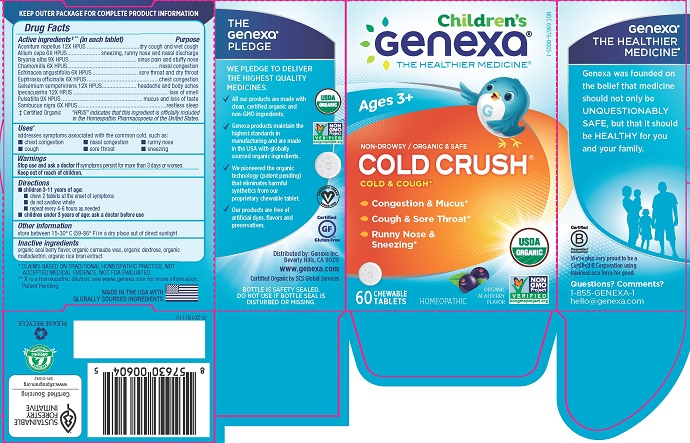 DRUG LABEL: Cold Crush Childrens
NDC: 69676-0005 | Form: TABLET, CHEWABLE
Manufacturer: Genexa Inc.
Category: homeopathic | Type: HUMAN OTC DRUG LABEL
Date: 20200611

ACTIVE INGREDIENTS: ONION 6 [hp_X]/1 1; BRYONIA ALBA ROOT 9 [hp_X]/1 1; MATRICARIA CHAMOMILLA WHOLE 6 [hp_X]/1 1; ECHINACEA ANGUSTIFOLIA 6 [hp_X]/1 1; EUPHRASIA STRICTA 6 [hp_X]/1 1; GELSEMIUM SEMPERVIRENS ROOT 12 [hp_X]/1 1; IPECAC 12 [hp_X]/1 1; PULSATILLA PRATENSIS 9 [hp_X]/1 1; SAMBUCUS NIGRA FLOWER 6 [hp_X]/1 1; ACONITUM NAPELLUS 12 [hp_X]/1 1
INACTIVE INGREDIENTS: CARNAUBA WAX; MALTODEXTRIN; RICE BRAN; DEXTROSE; ACAI

COLD CRUSH CHILDREN'S

KEEP OUTER PACKAGE FOR COMPLETE PRODUCT INFORMATION

Drug Facts

Active ingredients‡** (in each tablet)

Aconitum napellus 12X HPUS

Allum cepa 6X HPUS

Bryonia alba 9X HPUS

Chamomilla 6X HPUS

Echinacea angustifolia 6X HPUS

Euphrasia officinalis 6X HPUS

Gelsemium sempervirens 12X HPUS

Ipecacuanha 12X HPUS

Pulsatilla 9X HPUS

Sambucus nigra 6X HPUS

‡ Certified Organic

"HPUS" indicates that this ingredient is officially included in the Homeopathic Pharmacopoeia of the United States.

Purpose

dry cough and wet cough

sneezing, runny nose and nasal discharge

sinus pain and stuffy nose

nasal congestion

sore throat and dry throat

chest congestion

headache and body aches

loss of smell

mucus and loss of taste

restless sleep

Uses*

addresses symptoms associated with the common cold, such as:

- chest congestion
- nasal congestion
- runny nose
- cough
- sore throat
- sneezing

Warnings

Stop use and ask a doctor if symptoms persist for more than 3 days or worsen.

Keep out of reach of children.

Directions

- children 3-11 years of age:
- chew 2 tablets at the onset of symptoms
- do not swallow whole
- repeat every 4-6 hours as needed
- children under 3 years of age: ask a doctor before use

Other information

store between 15°-30°C (59°-86°F) in a dry place out of direct sunlight

Inactive ingredients

organic acai berry flavor, organic carnauba wax, organic dextrose, organic maltodextrin, organic rice bran extract

* CLAIMS BASED ON TRADITIONAL HOMEOPATHIC PRACTICE, NOT ACCEPTED MEDICAL EVIDENCE. NOT FDA EVALUATED.
** X is a homeopathic dilution: see www.genexa.com for more information.
Patent Pending

MADE IN THE USA WITH GLOBALLY SOURCED INGREDIENTS

THE Genexa® PLEDGE

WE PLEDGE TO DELIVER THE HIGHEST QUALITY MEDICINES.

All our products are made with clean, certified organic and non-GMO ingredients.

Genexa products maintain the highest standards in manufacturing and are made in the USA from globally sourced organic ingredients.

We pioneered the organic technology (patent pending) that eliminates harmful synthetics from our proprietary chewable tablet.

Our products are free of artificial dyes, flavors and preservatives.

Distributed by: Genexa Inc.

Beverly Hills, CA 90211

www.genexa.com

Certified Organic by SCS Global Services

BOTTLE IS SAFETY SEALED.

DO NOT USE IF BOTTLE SEAL IS DISTURBED OR MISSING.

Genexa®

THE HEALTHIER MEDICINE®

Genexa was founded on the belief that medicine should not only be UNQUESTIONABLY SAFE, but that it should be HEALTHY for you and your family.

We're also proud to be a Certified B Corporation using business as a force for good.

Questions? Comments?

1-855-GENEXA-1

hello@genexa.com

PACKAGE LABEL

Children's

Genexa®

THE HEALTHIER MEDICINE®

NDC 69676-0005-1

Ages 3+

NON-DROWSY / ORGANIC & SAFE

COLD CRUSH®

COLD & COUGH*

- Congestion & Mucus*
- Cough & Sore Throat*
- Runny Nose & Sneezing*

60 CHEWABLE TABLETS

HOMEOPATHIC

ORGANIC ACAI BERRY FLAVOR

USDA ORGANIC

NON GMO Project VERIFIED